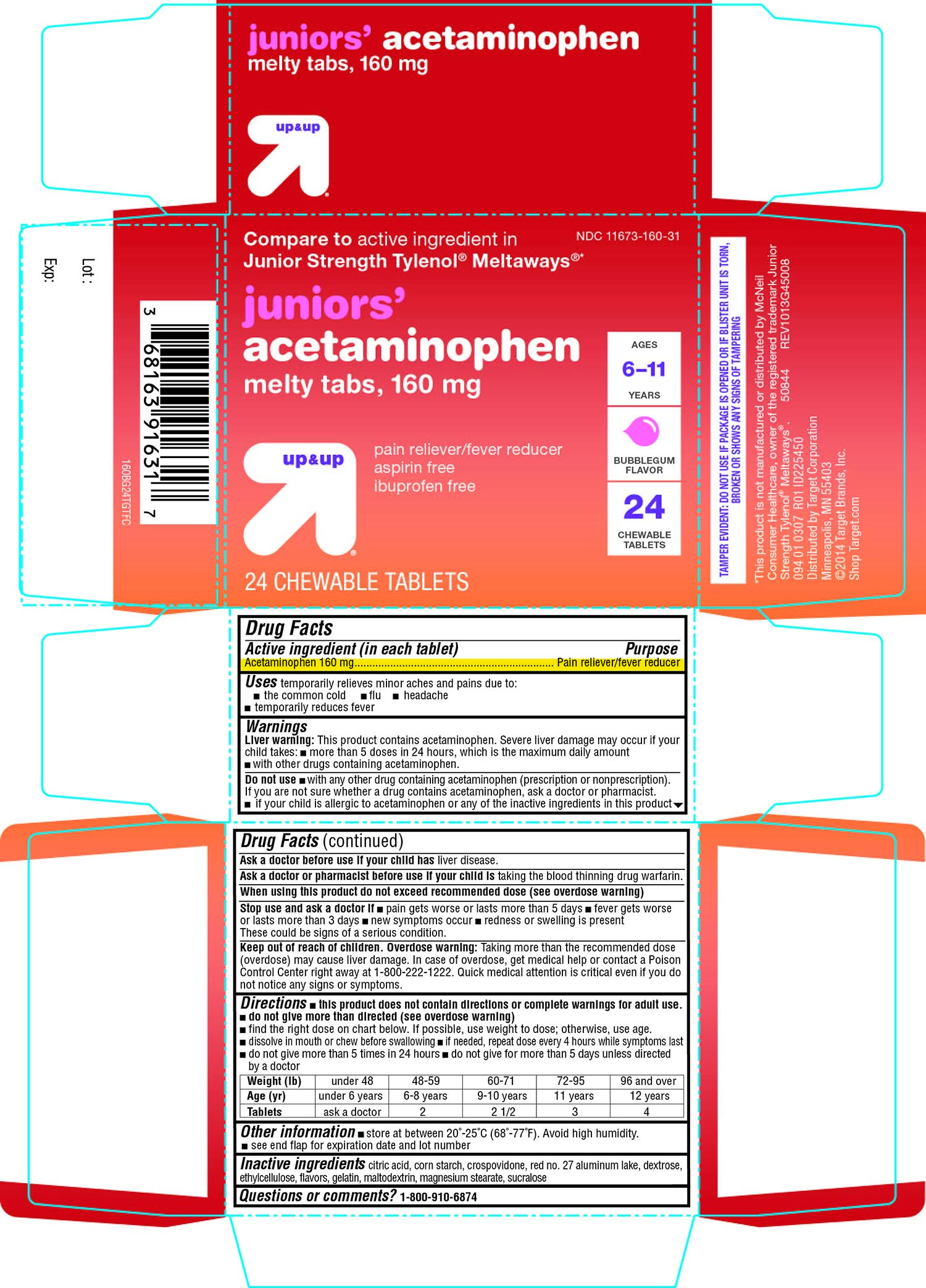 DRUG LABEL: up and up juniors acetaminophen
NDC: 11673-160 | Form: TABLET, CHEWABLE
Manufacturer: Target Corporation
Category: otc | Type: HUMAN OTC DRUG LABEL
Date: 20150116

ACTIVE INGREDIENTS: ACETAMINOPHEN 160 mg/1 1
INACTIVE INGREDIENTS: CITRIC ACID MONOHYDRATE; STARCH, CORN; CROSPOVIDONE; D&C RED NO. 27; DEXTROSE; ETHYLCELLULOSES; GELATIN; MALTODEXTRIN; MAGNESIUM STEARATE; SUCRALOSE

up and up juniors’ acetaminophen melty tabs

Active ingredient (in each tablet)

Acetaminophen 160 mg

Purpose

Pain reliever/fever reducer

Uses

- temporarily relieves minor aches and pains due to:
  - the common cold
  - flu
  - headache
- temporarily reduces fever

Warnings

Liver warning: This product contains acetaminophen. Severe liver damage may occur if your child takes:

- more than 5 doses in 24 hours, which is the maximum daily amount
- with other drugs containing acetaminophen.

Do not use

- with any other drug containing acetaminophen (prescription or nonprescription). If you are not sure whether a drug contains acetaminophen, ask a doctor or pharmacist.
- if your child is allergic to acetaminophen or any of the inactive ingredients in this product.

Ask a doctor before use if your child has

liver disease.

Ask a doctor or pharmacist before use if your child is

taking the blood thinning drug warfarin .

When using this product

do not exceed recommended dose (see overdose warning)

Stop use and ask a doctor if

- pain gets worse or lasts more than 5 days
- fever gets worse or lasts more than 3 days
- new symptoms occur
- redness or swelling is present

These could be signs of a serious condition.

Keep out of reach of children.

Overdose warning: Taking more than the recommended dose (overdose) may cause liver damage. In case of overdose, get medical help or contact a Poison Control Center right away at 1-800-222-1222. Quick medical attention is critical even if you do not notice any signs or symptoms.

Directions

- this product does not contain directions or complete warnings for adult use.
- do not give more than directed (see overdose warning)
- find the right dose on chart below. If possible, use weight to dose; otherwise use age.
- dissolve in mouth or chew before swallowing
- if needed, repeat dose every 4 hours while symptoms last
- do not give more than 5 times in 24 hours
- do not give for more than 5 days unless directed by a doctor

Weight (lb) | under 48 | 48-59 | 60-71 | 72-95 | 96 and over
Age (yr) | under 6 years | 6-8 years | 9-10 years | 11 years | 12 years
Tablets | ask a doctor | 2 | 2 1/2 | 3 | 4

Other information

- store at between 20º-25ºC (68º-77ºF). Avoid high humidity.
- see end flap for expiration date and lot number

Inactive ingredients

citric acid, corn starch, crospovidone, red no. 27 aluminum lake, dextrose, ethylcellulose, flavors, gelatin, maltodextrin, magnesium stearate, sucralose

Questions or comments ?

1-800-910-6874

Principal Display Panel

NDC 11673-160-31

Compare to active ingredient in Junior Strength Tylenol® Meltaways®*

juniors’

acetaminophen

melty tabs,160 mg

pain reliever/fever reducer

aspirin-free

ibuprofen-free

AGES 6-11 YEARS

BUBBLEGUM FLAVOR

24 CHEWABLE TABLETS

TAMPER EVIDENT: DO NOT USE IF PACKAGE IS OPENED OR IF BLISTER UNIT IS TORN, BROKEN OR SHOWS ANY SIGNS OF TAMPERING

*This product is not manufactured or distributed by McNeil Consumer Healthcare, owner of the registered trademark Junior Strength Tylenol® Meltaways®.

50844 REV1013G45008

094 01 0307 R01 ID225450

Distributed by Target Corporation

Minneapolis, MN 55403

© 2014 Target Brands, Inc.

Shop Target.com